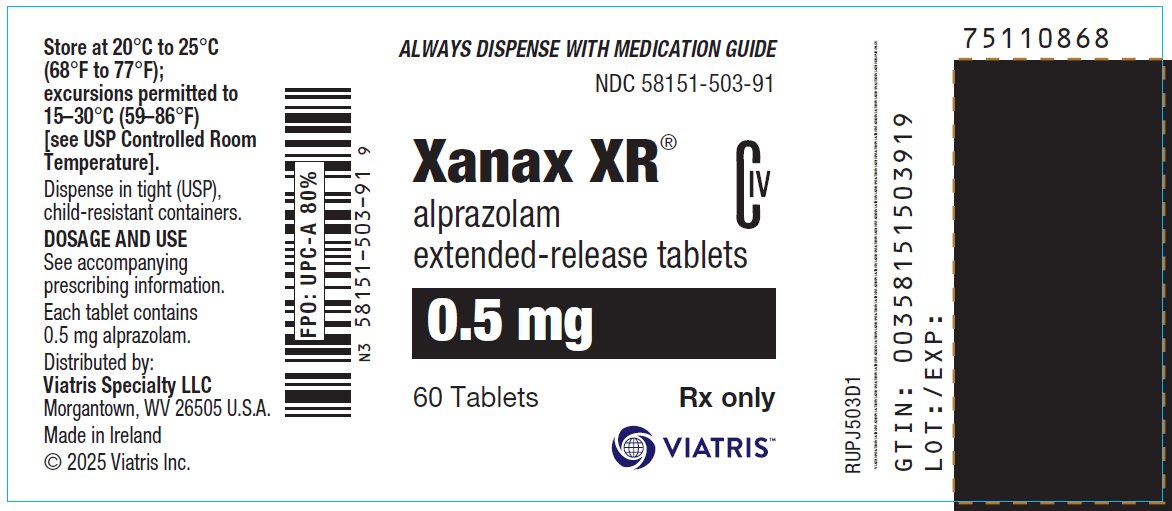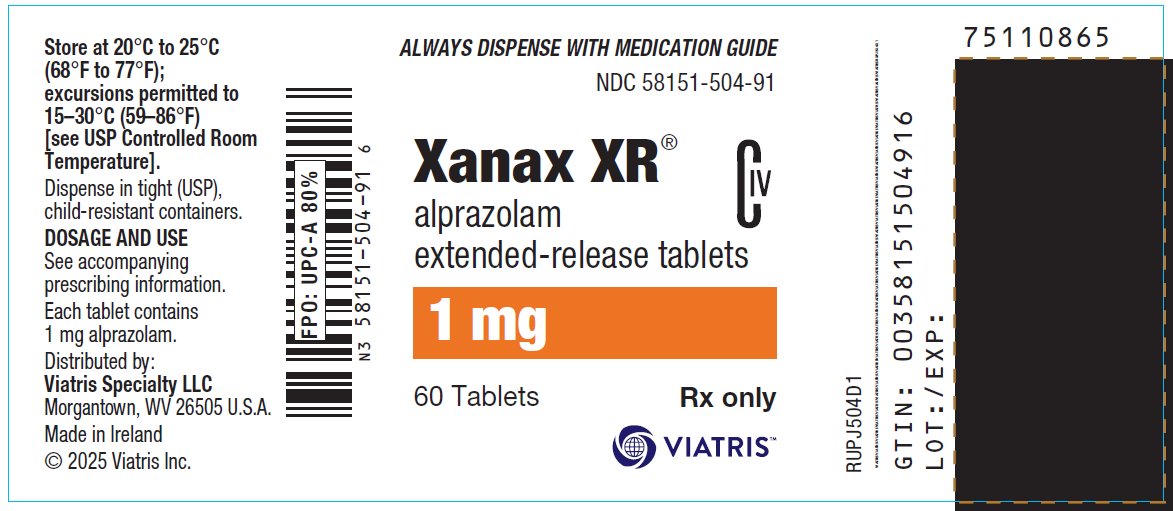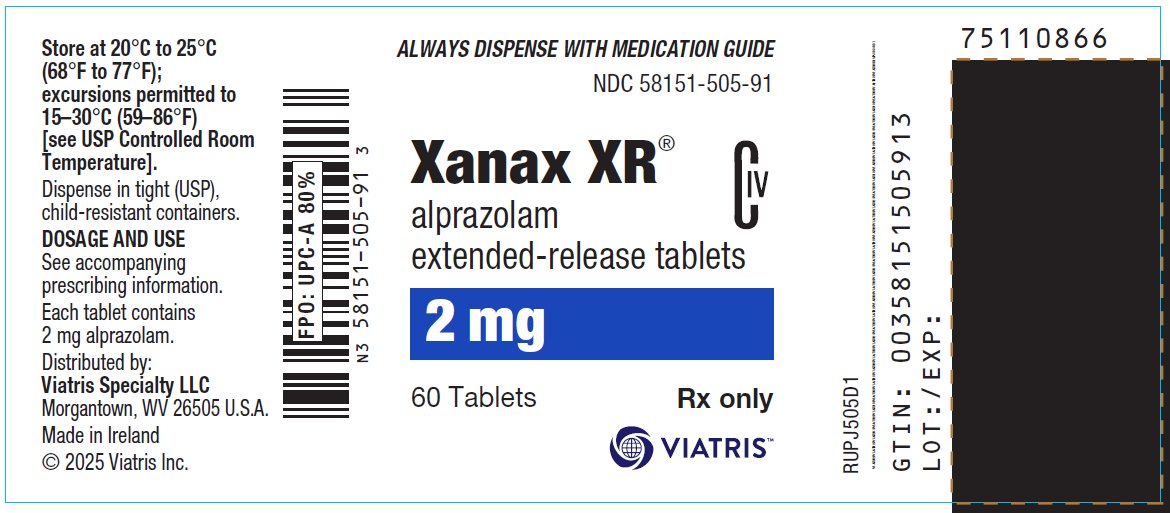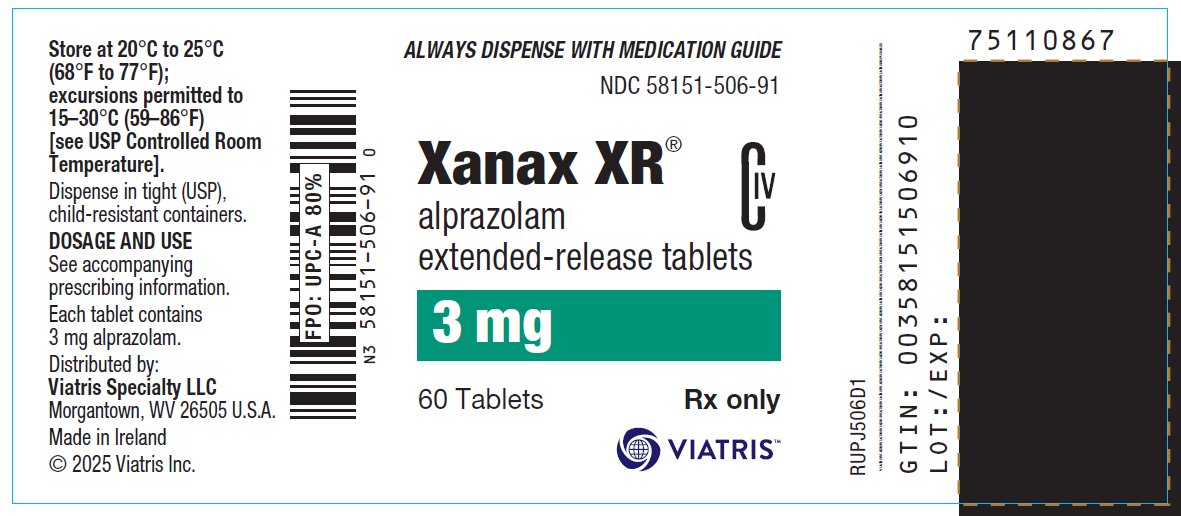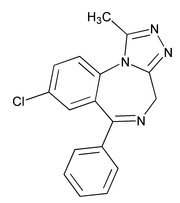 DRUG LABEL: Xanax
NDC: 58151-503 | Form: TABLET, EXTENDED RELEASE
Manufacturer: Viatris Specialty LLC
Category: prescription | Type: HUMAN PRESCRIPTION DRUG LABEL
Date: 20230412
DEA Schedule: CIV

ACTIVE INGREDIENTS: ALPRAZOLAM 0.5 mg/1 1
INACTIVE INGREDIENTS: SILICON DIOXIDE; HYPROMELLOSE, UNSPECIFIED; LACTOSE, UNSPECIFIED FORM; MAGNESIUM STEARATE

HIGHLIGHTS OF PRESCRIBING INFORMATION

These highlights do not include all the information needed to use XANAX XR safely and effectively. See full prescribing information for XANAX XR.
XANAX XR® (alprazolam) extended-release tablets, for oral use, CIV
Initial U.S. Approval: 1981

RECENT MAJOR CHANGES

Warnings and Precautions (5.8) 1/2023

WARNING: RISKS FROM CONCOMITANT USE WITH OPIOIDS; ABUSE, MISUSE, AND ADDICTION; and DEPENDENCE AND WITHDRAWAL REACTIONS

See full prescribing information for complete boxed warning.

- Concomitant use of benzodiazepines and opioids may result in profound sedation, respiratory depression, coma, and death. Reserve concomitant prescribing of these drugs for use in patients for whom alternative treatment options are inadequate. Limit dosages and durations to the minimum required. Follow patients for signs and symptoms of respiratory depression and sedation. (5.1, 7.1)
- The use of benzodiazepines, including XANAX XR, exposes users to risks of abuse, misuse, and addiction, which can lead to overdose or death. Before prescribing XANAX XR and throughout treatment, assess each patient’s risk for abuse, misuse, and addiction. (5.2)
- Abrupt discontinuation or rapid dosage reduction of XANAX XR after continued use may precipitate acute withdrawal reactions, which can be life-threatening. To reduce the risk of withdrawal reactions, use a gradual taper to discontinue XANAX XR or reduce the dosage. (2.2, 5.3)

1 INDICATIONS AND USAGE

XANAX XR is a benzodiazepine indicated for the treatment of panic disorder with or without agoraphobia, in adults. (1)

2 DOSAGE AND ADMINISTRATION

- Recommended starting oral dosage is 0.5 mg to 1 mg once daily (preferably in the morning). Depending on the response, the dose may be increased at intervals of 3 to 4 days in increments of no more than 1 mg daily. (2.1)
- Recommended total daily dosage is 3 mg to 6 mg daily. (2.1)
- Swallow tablets whole; do not divide, crush, or chew. (2.1)
- When tapering, decrease dosage by no more than 0.5 mg every 3 days. Some patients may require an even slower dosage reduction. (2.2, 5.2)
- See the Full Prescribing Information for the recommended dosage in geriatric patients, patients with hepatic impairment, and with use with ritonavir. (2.3, 2.4, 2.5)

3 DOSAGE FORMS AND STRENGTHS

Extended-Release Tablets: 0.5 mg, 1 mg, 2 mg, and 3 mg (3)

4 CONTRAINDICATIONS

- Known hypersensitivity to alprazolam or other benzodiazepines. (4)
- Concomitant use with strong cytochrome P450 3A (CYP3A) inhibitors, except ritonavir. (4, 5.5, 7.1)

5 WARNINGS AND PRECAUTIONS

- Effects on Driving and Operating Machinery: Patients receiving XANAX XR should be cautioned against operating machinery or driving a motor vehicle, as well as avoiding concomitant use of alcohol and other central nervous system (CNS) depressant drugs. (5.4)
- Patients with Depression: Exercise caution in patients with signs or symptoms of depression. Prescribe the least number of tablets feasible to avoid intentional overdosage. (5.6)
- Neonatal Sedation and Withdrawal Syndrome: XANAX XR use during pregnancy can result in neonatal sedation and/or neonatal withdrawal. (5.8, 8.1)

6 ADVERSE REACTIONS

The most common adverse reactions in panic disorder patients treated with XANAX XR (incidence of ≥ 5% and at least twice that of placebo) include: somnolence, memory impairment, dysarthria, coordination abnormal, ataxia, libido decreased, constipation, and nausea. (6.1)

To report SUSPECTED ADVERSE REACTIONS, contact Viatris at 1-877-446-3679 (1-877-4-INFO-RX) or FDA at 1-800-FDA-1088 or www.fda.gov/medwatch.

7 DRUG INTERACTIONS

- Use with Opioids: Increase the risk of respiratory depression. (7.1)
- Use with Other CNS Depressants: Produces additive CNS depressant effects. (7.1)
- Use with Digoxin: Increase the risk of digoxin toxicity. (7.1)
- Use with CYP3A Inhibitors (except ritonavir): Increase the risk of adverse reactions of alprazolam. (4, 5.5, 7.1)
- Use with CYP3A Inducers: Increase the risk of reduced efficacy of alprazolam. (7.1)

8 USE IN SPECIFIC POPULATIONS

Lactation: Breastfeeding not recommended. (8.2)

FULL PRESCRIBING INFORMATION

WARNING: RISKS FROM CONCOMITANT USE WITH OPIOIDS; ABUSE, MISUSE, AND ADDICTION; and DEPENDENCE AND WITHDRAWAL REACTIONS

- Concomitant use of benzodiazepines and opioids may result in profound sedation, respiratory depression, coma, and death. Reserve concomitant prescribing of these drugs for patients for whom alternative treatment options are inadequate. Limit dosages and durations to the minimum required. Follow patients for signs and symptoms of respiratory depression and sedation [see Warnings and Precautions (5.1), Drug Interactions (7.1)].
- The use of benzodiazepines, including XANAX XR, exposes users to risks of abuse, misuse, and addiction, which can lead to overdose or death. Abuse and misuse of benzodiazepines commonly involve concomitant use of other medications, alcohol, and/or illicit substances, which is associated with an increased frequency of serious adverse outcomes. Before prescribing XANAX XR and throughout treatment, assess each patient’s risk for abuse, misuse, and addiction [see Warnings and Precautions (5.2)].
- The continued use of benzodiazepines, including XANAX XR, may lead to clinically significant physical dependence. The risks of dependence and withdrawal increase with longer treatment duration and higher daily dose. Abrupt discontinuation or rapid dosage reduction of XANAX XR after continued use may precipitate acute withdrawal reactions, which can be life-threatening. To reduce the risk of withdrawal reactions, use a gradual taper to discontinue XANAX XR or reduce the dosage [see Dosage and Administration (2.2), Warnings and Precautions (5.3)].

1 INDICATIONS AND USAGE

XANAX XR is indicated for the treatment of panic disorder with or without agoraphobia, in adults.

2 DOSAGE AND ADMINISTRATION

2.1 Recommended Dosage

Administer XANAX XR orally once daily, preferably in the morning. Swallow tablets whole; do not divide, crush, or chew.

The recommended starting oral dosage for XANAX XR is 0.5 mg to 1 mg once daily. Depending on the response, the dosage may be adjusted at intervals of every 3 to 4 days in increments of no more than 1 mg daily. The recommended dosage range is 3 mg to 6 mg once daily.

Controlled trials of XANAX XR for the treatment of panic disorder included dosages in the range of 1 mg to 10 mg per day. Most patients showed a response in the dosage range of 3 mg to 6 mg per day. Occasional patients required as much as 10 mg per day.

The longer term efficacy of XANAX XR has not been systematically evaluated. If XANAX XR is used for periods longer than 8 weeks, the healthcare provider should periodically reassess the usefulness of the drug for the individual patient.

After a period of extended freedom from panic attacks, a carefully supervised tapered discontinuation may be attempted, but there is evidence that this may often be difficult to accomplish without recurrence of symptoms and/or the manifestation of withdrawal phenomena [see Dosage and Administration (2.2), Warnings and Precautions (5.2)].

2.2 Discontinuation or Dosage Reduction of XANAX XR

To reduce the risk of withdrawal reactions, use a gradual taper to discontinue XANAX XR or reduce the dosage. If a patient develops withdrawal reactions, consider pausing the taper or increasing the dosage to the previous tapered dosage level. Subsequently decrease the dosage more slowly [see Warnings and Precautions (5.3), Drug Abuse and Dependence (9.3)].

Reduce the dosage by no more than 0.5 mg every three days. Some patients may benefit from an even more gradual discontinuation. Some patients may prove resistant to all discontinuation regimens.

In a controlled postmarketing discontinuation study of panic disorder patients which compared the recommended taper schedule with a slower taper schedule, no difference was observed between the groups in the proportion of patients who tapered to zero dose; however, the slower schedule was associated with a reduction in symptoms associated with a withdrawal syndrome.

2.3 Dosage Recommendations in Geriatric Patients

In geriatric patients, the recommended starting dosage of XANAX XR is 0.5 mg once daily. This may be gradually increased if needed and tolerated. Geriatric patients may be sensitive to the effects of benzodiazepines [see Use in Specific Populations (8.5), Clinical Pharmacology (12.3)].

2.4 Dosage Recommendations in Patients with Hepatic Impairment

In patients with hepatic impairment, the recommended starting dosage of XANAX XR is 0.5 mg once daily. This may be gradually increased if needed and tolerated [see Use in Specific Populations (8.6), Clinical Pharmacology (12.3)].

2.5 Dosage Modifications for Drug Interactions

XANAX XR should be reduced to half of the recommended dosage when a patient is started on ritonavir and XANAX XR together, or when ritonavir is added to a patient treated with XANAX XR. Increase XANAX XR dosage to the target dose after 10 to 14 days of dosing ritonavir and XANAX XR together. It is not necessary to reduce XANAX XR dosage in patients who have been taking ritonavir for more than 10 to 14 days.

XANAX XR is contraindicated with concomitant use of all strong CYP3A inhibitors, except ritonavir [see Contraindications (4), Warnings and Precautions (5.5), Drug Interactions (7.1)].

2.6 Switching Patients from XANAX Tablets to XANAX XR Tablets

Patients who are currently being treated with divided doses of XANAX may be switched to XANAX XR at the same total daily dose taken once daily. If the clinical response after switching is inadequate, titrate the dosage as outlined above.

3 DOSAGE FORMS AND STRENGTHS

XANAX XR extended-release tablets are available as:

- 0.5 mg: white, pentagonal shaped tablets debossed with an "X" on one side and "0.5" on the other side
- 1 mg: yellow, square shaped tablets debossed with an "X" on one side and "1" on the other side
- 2 mg: blue, round shaped tablets debossed with an "X" on one side and "2" on the other side
- 3 mg: green, triangular shaped tablets debossed with an "X" on one side and "3" on the other side

4 CONTRAINDICATIONS

XANAX XR is contraindicated in patients:

- with known hypersensitivity to alprazolam or other benzodiazepines. Angioedema has been reported [see Adverse Reactions (6.2)].
- taking strong cytochrome P450 3A (CYP3A) inhibitors (e.g., ketoconazole, itraconazole), except ritonavir [see Dosage and Administration (2.5), Warnings and Precautions (5.5), Drug Interactions (7.1)].

5 WARNINGS AND PRECAUTIONS

5.1 Risks from Concomitant Use with Opioids

Concomitant use of benzodiazepines, including XANAX XR, and opioids may result in profound sedation, respiratory depression, coma, and death. Because of these risks, reserve concomitant prescribing of these drugs in patients for whom alternative treatment options are inadequate.

Observational studies have demonstrated that concomitant use of opioid analgesics and benzodiazepines increases the risk of drug-related mortality compared to use of opioids alone. If a decision is made to prescribe XANAX XR concomitantly with opioids, prescribe the lowest effective dosages and minimum durations of concomitant use, and follow patients closely for signs and symptoms of respiratory depression and sedation. In patients already receiving an opioid analgesic, prescribe a lower initial dose of XANAX XR than indicated in the absence of an opioid and titrate based on clinical response. If an opioid is initiated in a patient already taking XANAX XR, prescribe a lower initial dose of the opioid and titrate based upon clinical response.

Advise both patients and caregivers about the risks of respiratory depression and sedation when XANAX XR is used with opioids. Advise patients not to drive or operate heavy machinery until the effects of concomitant use with the opioid have been determined [see Drug Interactions (7.1)].

5.2 Abuse, Misuse, and Addiction

The use of benzodiazepines, including XANAX XR, exposes users to the risks of abuse, misuse, and addiction, which can lead to overdose or death. Abuse and misuse of benzodiazepines often (but not always) involve the use of doses greater than the maximum recommended dosage and commonly involve concomitant use of other medications, alcohol, and/or illicit substances, which is associated with an increased frequency of serious adverse outcomes, including respiratory depression, overdose, or death [see Drug Abuse and Dependence (9.2)].

Before prescribing XANAX XR and throughout treatment, assess each patient’s risk for abuse, misuse, and addiction (e.g., using a standardized screening tool). Use of XANAX XR, particularly in patients at elevated risk, necessitates counseling about the risks and proper use of XANAX XR along with monitoring for signs and symptoms of abuse, misuse, and addiction. Prescribe the lowest effective dosage; avoid or minimize concomitant use of CNS depressants and other substances associated with abuse, misuse, and addiction (e.g., opioid analgesics, stimulants); and advise patients on the proper disposal of unused drug. If a substance use disorder is suspected, evaluate the patient and institute (or refer them for) early treatment, as appropriate.

5.3 Dependence and Withdrawal Reactions

To reduce the risk of withdrawal reactions, use a gradual taper to discontinue XANAX XR or reduce the dosage (a patient-specific plan should be used to taper the dose) [see Dosage and Administration (2.3)].

Patients at an increased risk of withdrawal adverse reactions after benzodiazepine discontinuation or rapid dosage reduction include those who take higher dosages, and those who have had longer durations of use.

Acute Withdrawal Reactions

The continued use of benzodiazepines, including XANAX XR, may lead to clinically significant physical dependence. Abrupt discontinuation or rapid dosage reduction of XANAX XR after continued use, or administration of flumazenil (a benzodiazepine antagonist) may precipitate acute withdrawal reactions, which can be life-threatening (e.g., seizures) [see Drug Abuse and Dependence (9.3)].

Protracted Withdrawal Syndrome

In some cases, benzodiazepine users have developed a protracted withdrawal syndrome with withdrawal symptoms lasting weeks to more than 12 months [see Drug Abuse and Dependence (9.3)].

Certain adverse clinical events, some life-threatening, are a direct consequence of physical dependence to XANAX XR. These include a spectrum of withdrawal symptoms; the most important is seizure [see Drug Abuse and Dependence (9.3)]. Even after relatively short-term use at doses of ≤ 4 mg/day, there is some risk of dependence. Spontaneous reporting system data suggest that the risk of dependence and its severity appear to be greater in patients treated with doses greater than 4 mg/day and for long periods (more than 12 weeks). However, in a controlled postmarketing discontinuation study of panic disorder patients who received XANAX, the duration of treatment (3 months compared to 6 months) had no effect on the ability of patients to taper to zero dose. In contrast, patients treated with doses of XANAX greater than 4 mg/day had more difficulty tapering to zero dose than those treated with less than 4 mg/day.

In a controlled clinical trial in which 63 patients were randomized to XANAX and where withdrawal symptoms were specifically sought, the following were identified as symptoms of withdrawal: heightened sensory perception, impaired concentration, dysosmia, clouded sensorium, paresthesias, muscle cramps, muscle twitch, diarrhea, blurred vision, appetite decrease, and weight loss. Other symptoms, such as anxiety and insomnia, were frequently seen during discontinuation, but it could not be determined if they were due to return of illness, rebound, or withdrawal.

Interdose Symptoms

Early morning anxiety and emergence of anxiety symptoms between doses of XANAX have been reported in patients with panic disorder taking prescribed maintenance doses. These symptoms may reflect the development of tolerance or a time interval between doses which is longer than the duration of clinical action of the administered dose. In either case, it is presumed that the prescribed dose is not sufficient to maintain plasma levels above those needed to prevent relapse, rebound, or withdrawal symptoms over the entire course of the interdosing interval.

5.4 Effects on Driving and Operating Machinery

Because of its CNS depressant effects, patients receiving XANAX XR should be cautioned against engaging in hazardous occupations or activities requiring complete mental alertness such as operating machinery or driving a motor vehicle. For the same reason, patients should be cautioned about the concomitant use of alcohol and other CNS depressant drugs during treatment with XANAX XR [see Drug Interactions (7.1)].

5.5 Interaction with Drugs that Inhibit Metabolism via Cytochrome P450 3A

The initial step in alprazolam metabolism is hydroxylation catalyzed by cytochrome P450 3A (CYP3A). Drugs that inhibit this metabolic pathway may have a profound effect on the clearance of alprazolam.

Strong CYP3A Inhibitors

XANAX XR is contraindicated in patients receiving strong inhibitors of CYP3A such as azole antifungal agents [see Contraindications (4)]. Ketoconazole and itraconazole have been shown in vivo to increase plasma alprazolam concentrations 3.98 fold and 2.70 fold, respectively.

Dosage adjustment is necessary when XANAX XR and ritonavir are initiated concomitantly or when ritonavir is added to a stable dosage of XANAX XR [see Dosage and Administration (2.5), Drug Interactions (7.1)].

Drugs demonstrated to be CYP3A inhibitors on the basis of clinical studies involving alprazolam: nefazodone, fluvoxamine, and cimetidine [see Drug Interaction (7.1), Clinical Pharmacology (12.3)]. Use caution and consider dose reduction of XANAX XR, as appropriate, during co-administration with these drugs.

5.6 Patients with Depression

Benzodiazepines may worsen depression. Panic disorder has been associated with primary and secondary major depressive disorders and increased reports of suicide among untreated patients. Consequently, appropriate precautions (e.g., limiting the total prescription size and increased monitoring for suicidal ideation) should be considered in patients with depression.

5.7 Mania

Episodes of hypomania and mania have been reported in association with the use of XANAX XR in patients with depression [see Adverse Reactions (6.1)].

5.8 Neonatal Sedation and Withdrawal Syndrome

Use of XANAX XR late in pregnancy can result in sedation (respiratory depression, lethargy, hypotonia) and/or withdrawal symptoms (hyperreflexia, irritability, restlessness, tremors, inconsolable crying, and feeding difficulties) in the neonate [see Use in Specific Populations (8.1)]. Monitor neonates exposed to XANAX XR during pregnancy or labor for signs of sedation and monitor neonates exposed to XANAX XR during pregnancy for signs of withdrawal; manage these neonates accordingly.

5.9 Risks in Patients with Impaired Respiratory Function

There have been reports of death in patients with severe pulmonary disease shortly after the initiation of treatment with alprazolam. Closely monitor patients with impaired respiratory function. If signs and symptoms of respiratory depression, hypoventilation, or apnea occur, discontinue XANAX XR.

6 ADVERSE REACTIONS

The following clinically significant adverse reactions are described elsewhere in the labeling:

- Risks from Concomitant Use with Opioids [see Warnings and Precautions (5.1)]
- Abuse, Misuse, and Addiction [see Warnings and Precautions (5.2)]
- Dependence and Withdrawal Reactions [see Warnings and Precautions (5.3)]
- Effects on Driving and Operating Machinery [see Warnings and Precautions (5.4)]
- Patients with Depression [see Warnings and Precautions (5.7)]
- Neonatal Sedation and Withdrawal Syndrome [see Warnings and Precautions (5.8)]
- Risks in Patients with Impaired Respiratory Function [see Warnings and Precautions (5.9)]

6.1 Clinical Trials Experience

Because clinical trials are conducted under widely varying conditions, adverse reaction rates observed in the clinical trials of a drug cannot be directly compared to rates in the clinical trials of another drug and may not reflect the rates observed in practice.

The information included in the section on Adverse Reactions Observed in Short-Term, Placebo-Controlled Trials with XANAX XR is based on pooled data of five 6- and 8-week placebo-controlled clinical studies in panic disorder.

Adverse Reactions Observed in Short-Term, Placebo-Controlled Trials of XANAX XR

Adverse Reactions Reported as Reasons for Discontinuation of Treatment in Placebo-Controlled Trials

Approximately 17% of the 531 patients who received XANAX XR in placebo-controlled clinical trials for panic disorder had at least 1 adverse event that led to discontinuation compared to 8% of 349 placebo-treated patients. The most common events leading to discontinuation and considered to be drug-related (i.e., leading to discontinuation in at least 1% of the patients treated with XANAX XR at a rate at least twice that of placebo) are shown in Table 1.

Table 1: Adverse Reactions Leading to Discontinuation in ≥1% of XANAX XR-Treated Patients and at Least Twice the Rate of Placebo-Treated Patients in Placebo-Controlled Trials
 | Percentage of Patients Discontinuing Due to Adverse Reactions
 | XANAX XR (n=531) | Placebo (n=349)
Nervous system disorders Sedation Somnolence Dysarthria Coordination abnormal Memory impairment | 7.5 3.2 2.1 1.9 1.5 | 0.6 0.3 0 0.3 0.3
General disorders/administration site conditions Fatigue | 1.7 | 0.6
Psychiatric disorders Depression | 2.5 | 1.2
n=number of patients

Adverse Reactions Occurring at an Incidence of 1% or More Among Patients Treated with XANAX XR

Table 2 shows the incidence of adverse reactions that occurred during 6- and 8-week placebo-controlled trials in 1% or more of patients treated with XANAX XR where the incidence in patients treated with XANAX XR was greater than the incidence in placebo-treated patients. The most commonly observed adverse reactions in panic disorder patients treated with XANAX XR (incidence of 5% or greater and at least twice the incidence in placebo patients) were: sedation, somnolence, memory impairment, dysarthria, coordination abnormal, ataxia, libido decreased.

Table 2: Adverse Reactions Occurring in ≥ 1% in XANAX-Treated Patients and Greater than Placebo-Treated Patients in 6- and 8-Week Placebo-Controlled Trials Panic Disorder
 | XANAX XR (n=531) | Placebo (n=349)
Nervous system disorders Sedation Somnolence Memory impairment Dysarthria Coordination abnormal Mental impairment Ataxia Disturbance in attention Balance impaired Dyskinesia Hypoesthesia Hypersomnia | 45% 23% 15% 11% 9% 7% 7% 3% 3% 2% 1% 1% | 23% 6% 7% 3% 1% 6% 3% 1% 1% 1% <1% 0%
General disorders/administration site conditions Fatigue Lethargy | 14% 2% | 9% 1%
Psychiatric disorders Depression Libido decreased Disorientation Confusion Depressed mood | 12% 6% 2% 2% 1% | 9% 2% 0% 1% <1%
Metabolism and nutrition disorders Appetite increased Anorexia | 7% 2% | 6% 0%
Gastrointestinal disorders Constipation Nausea | 8% 6% | 4% 3%
Investigations Weight increased | 5 | 4
Injury, poisoning, and procedural complications Road traffic accident | 2% | 0%
Reproductive system and breast disorders Dysmenorrhea Sexual dysfunction | 4% 2% | 3% 1%
Musculoskeletal and connective tissue disorder Arthralgia Myalgia Pain in limb | 2% 2% 1% | 1% 1% 0%
Respiratory, thoracic, and mediastinal disorders Dyspnea | 2% | 0%

Other Adverse Reactions Observed During the Premarketing Evaluation of XANAX XR

Following is a list of other adverse reaction reported by 531 patients with panic disorder treated with XANAX XR. Adverse reactions are further categorized by body system and listed in order of decreasing frequency according to the following definitions: those occurring in at least 1/100 patients (frequent); those occurring in less than 1/100 patients but at least 1/1000 patients (infrequent); those occurring in fewer than 1/1000 patients (rare).

Cardiac disorders: Frequent: palpitation; Infrequent: sinus tachycardia

Ear and labyrinth disorders: Frequent: vertigo; Infrequent: tinnitus, ear pain

Eye disorders: Frequent: blurred vision; Infrequent: mydriasis, photophobia

Gastrointestinal disorders: Frequent: diarrhea, vomiting, dyspepsia, abdominal pain; Infrequent: dysphagia, salivary hypersecretion

General disorders and administration site conditions: Frequent: malaise, weakness, chest pains; Infrequent: fall, pyrexia, thirst, feeling hot and cold, edema, feeling jittery, sluggishness, asthenia, feeling drunk, chest tightness, increased energy, feeling of relaxation, hangover, loss of control of legs, rigors

Musculoskeletal and connective tissue disorders: Frequent: back pain, muscle cramps, muscle twitching

Nervous system disorders: Frequent: headache, dizziness, tremor; Infrequent: amnesia, clumsiness, syncope, hypotonia, seizures, depressed level of consciousness, sleep apnea syndrome, sleep talking, stupor

Psychiatric system disorders: Frequent: irritability, insomnia, nervousness, derealization, libido increased, restlessness, agitation, depersonalization, nightmare; Infrequent: abnormal dreams, apathy, aggression, anger, bradyphrenia, euphoric mood, logorrhea, mood swings, dysphonia, hallucination, homicidal ideation, mania, hypomania, impulse control, psychomotor retardation, suicidal ideation

Renal and urinary disorders: Frequent: difficulty in micturition; Infrequent: urinary frequency, urinary incontinence

Respiratory, thoracic, and mediastinal disorders: Frequent: nasal congestion, hyperventilation; Infrequent: choking sensation, epistaxis, rhinorrhea

Skin and subcutaneous tissue disorders: Frequent: sweating increased; Infrequent: clamminess, rash, urticaria

Vascular disorders: Infrequent: hypotension

Discontinuation-Emergent Adverse Reactions Occurring at an Incidence of 5% or More Among Patients Treated with XANAX XR

Table 3 shows the incidence of discontinuation-emergent adverse reactions that occurred during short-term, placebo-controlled trials in 5% or more of patients treated with XANAX XR where the incidence in patients treated with XANAX XR was 2 times greater than the incidence in placebo-treated patients.

Table 3: Discontinuation-Emergent Symptom Incidence Reported in ≥5% of XANAX XR-Treated Patients and at Least Twice the Rate of Placebo-Treated Patients in Short-Term, Placebo-Controlled Trials
 | XANAX XR n=422 (%) | Placebo n=261(%)
Nervous system disorders; Tremor; Headache; Hypoesthesia; Paresthesia | 28.2 26.5 7.8 7.1 | 10.7 12.6 2.3 2.7
Psychiatric disorders; Insomnia; Nervousness; Depression; Derealization; Anxiety; Depersonalization | 24.2 21.8 10.9 8.0 7.8 5.7 | 9.6 8.8 5.0 3.8 2.7 1.9
Gastrointestinal disorders Diarrhea | 12.1 | 3.1
Respiratory, thoracic and mediastinal disorders Hyperventilation | 8.5 | 2.7
Metabolism and nutrition disorders Appetite decreased | 9.5 | 3.8
Musculoskeletal and connective tissue disorders Muscle twitching | 7.4 | 2.7
Vascular disorders Hot flushes | 5.9 | 2.7

There have also been reports of withdrawal seizures upon rapid decrease or abrupt discontinuation of XANAX [see Warning and Precautions (5.2), Drug Abuse and Dependence (9.3)].

Paradoxical reactions such as stimulation, increased muscle spasticity, sleep disturbances, hallucinations, and other adverse behavioral effects such as agitation, rage, irritability, and aggressive or hostile behavior have been reported rarely. In many of the spontaneous case reports of adverse behavioral effects, patients were receiving other CNS drugs concomitantly and/or were described as having underlying psychiatric conditions. Should any of the above events occur, alprazolam should be discontinued. Isolated published reports involving small numbers of patients have suggested that patients who have borderline personality disorder, a prior history of violent or aggressive behavior, or alcohol or substance abuse may be at risk for such events. Instances of irritability, hostility, and intrusive thoughts have been reported during discontinuation of alprazolam in patients with posttraumatic stress disorder.

6.2 Postmarketing Experience

The following adverse reactions have been identified during post-approval use of XANAX and/or XANAX XR. Because these reactions are reported voluntarily from a population of uncertain size, it is not always possible to reliably estimate their frequency or establish a causal relationship to drug exposure.

Endocrine disorders: Hyperprolactinemia

General disorders and administration site conditions: Edema peripheral

Hepatobiliary disorders: Hepatitis, hepatic failure, jaundice

Investigations: Liver enzyme elevations

Psychiatric disorders: Hypomania, mania

Reproductive system and breast disorders: Gynecomastia, galactorrhea, menstruation irregular

Skin and subcutaneous tissue disorders: Photosensitivity reaction, angioedema, Stevens-Johnson syndrome

7 DRUG INTERACTIONS

7.1 Drugs Having Clinically Important Interactions with XANAX XR

Table 4 includes clinically significant drug interactions with XANAX XR [see Clinical Pharmacology (12.3)].

Table 4: Clinically Significant Drug Interactions with XANAX XR
Opioids
Clinical implication | The concomitant use of benzodiazepines and opioids increases the risk of respiratory depression because of actions at different receptor sites in the CNS that control respiration. Benzodiazepines interact at gamma-aminobutyric acid (GABAA) sites and opioids interact primarily at mu receptors. When benzodiazepines and opioids are combined, the potential for benzodiazepines to significantly worsen opioid-related respiratory depression exists.
Prevention or management | Limit dosage and duration of concomitant use of XANAX XR and opioids, and monitor patients closely for respiratory depression and sedation [see Warnings and Precautions (5.1)].
Examples | Morphine, buprenorphine, hydromorphone, oxymorphone, oxycodone, fentanyl, methadone, alfentanil, butorphanol, codeine, dihydrocodeine, meperidine, pentazocine, remifentanil, sufentanil, tapentadol, tramadol.
CNS Depressants
Clinical implication | The benzodiazepines, including alprazolam, produce additive CNS depressant effects when coadministered with other CNS depressants.
Prevention or management | Limit dosage and duration of XANAX XR during concomitant use with CNS depressants [see Warnings and Precautions (5.3)].
Examples | Psychotropic medications, anticonvulsants, antihistaminics, ethanol, and other drugs which themselves produce CNS depression.
Strong Inhibitors of CYP3A (except ritonavir)
Clinical implication | Concomitant use of XANAX XR with strong CYP3A inhibitors has a profound effect on the clearance of alprazolam, resulting in increased concentrations of alprazolam and increased risk of adverse reactions [see Clinical Pharmacology (12.3)].
Prevention or management | Concomitant use of XANAX XR with a strong CYP3A4 inhibitor (except ritonavir) is contraindicated [see Contraindications (4), Warnings and Precautions (5.5)].
Examples | Ketoconazole, itraconazole, clarithromycin
Moderate or Weak Inhibitors of CYP3A
Clinical implication | Concomitant use of XANAX XR with CYP3A inhibitors may increase the concentrations of XANAX XR, resulting in increased risk of adverse reactions [see Clinical Pharmacology (12.3)].
Prevention or management | Avoid use and consider appropriate dose reduction when XANAX XR is coadministered with a moderate or weak CYP3A inhibitor [see Warnings and Precautions (5.5)].
Examples | Nefazodone, fluvoxamine, cimetidine, erythromycin
CYP3A Inducers
Clinical implication | Concomitant use of CYP3A inducers can increase alprazolam metabolism and therefore can decease plasma levels of alprazolam [see Clinical Pharmacology (12.3)].
Prevention or management | Caution is recommended during coadministration with alprazolam.
Examples | Carbamazepine, phenytoin
Ritonavir
Clinical implication | Interactions involving ritonavir and alprazolam are complex and time dependent. Short term administration of ritonavir increased alprazolam exposure due to CYP3A4 inhibition. Following long term treatment of ritonavir (> 10-14 days), CYP3A4 induction offsets this inhibition.; Alprazolam exposure was not meaningfully affected in the presence of ritonavir.
Prevention or management | Reduce XANAX XR dose when a patient is initiated with ritonavir and XANAX XR concomitantly, or when ritonavir is added to a regimen where XANAX XR is stabilized.; Increase XANAX XR dosage to the target dosage after 10 to 14 days of dosing ritonavir and XANAX XR concomitantly. No dosage adjustment of XANXR XR is necessary in patients receiving ritonavir for more than 10 to 14 days [see Dosage and Administration (2.5)].; Concomitant use of XANAX XR with a strong CYP3A inhibitor, except ritonavir, is contraindicated [see Contraindications (4), Warnings and Precautions (5.5)].
Digoxin
Clinical implication | Increased digoxin concentrations have been reported when alprazolam was given, especially in geriatric patients (>65 years of age).
Prevention or management | In patients on digoxin therapy, measure serum digoxin concentrations before initiating XANAX XR. Continue monitoring digoxin serum concentration and toxicity frequently. Reduce the digoxin dose if necessary.

7.2 Drug/Laboratory Test Interactions

Although interactions between benzodiazepines and commonly employed clinical laboratory tests have occasionally been reported, there is no consistent pattern for a specific drug or specific test.

8 USE IN SPECIFIC POPULATIONS

8.1 Pregnancy

Pregnancy Exposure Registry

There is a pregnancy exposure registry that monitors pregnancy outcomes in women exposed to psychiatric medications, including XANAX XR, during pregnancy. Healthcare providers are encouraged to register patients by calling the National Pregnancy Registry for Psychiatric Medications at 1-866-961-2388 or visiting online at https://womensmentalhealth.org/pregnancyregistry/.

Risk Summary

Neonates born to mothers using benzodiazepines late in pregnancy have been reported to experience symptoms of sedation and/or neonatal withdrawal [see Warnings and Precautions (5.8), and Clinical Considerations]. Available data from published observational studies of pregnant women exposed to benzodiazepines do not report a clear association with benzodiazepines and major birth defects (see Data).

The background risk of major birth defects and miscarriage for the indicated population is unknown. All pregnancies have a background risk of birth defect, loss, or other adverse outcomes. In the U.S. general population, the estimated risk of major birth defects and of miscarriage in clinically recognized pregnancies is 2% to 4% and 15% to 20%, respectively.

Clinical Considerations

Fetal/Neonatal Adverse Reactions

Benzodiazepines cross the placenta and may produce respiratory depression, hypotonia, and sedation in neonates. Monitor neonates exposed to XANAX XR during pregnancy or labor for signs of sedation, respiratory depression, hypotonia, and feeding problems. Monitor neonates exposed to XANAX XR during pregnancy for signs of withdrawal. Manage these neonates accordingly [see Warnings and Precautions (5.8)].

Data

Human Data

Published data from observational studies on the use of benzodiazepines during pregnancy do not report a clear association with benzodiazepines and major birth defects. Although early studies reported an increased risk of congenital malformations with diazepam and chlordiazepoxide, there was no consistent pattern noted. In addition, the majority of recent case-control and cohort studies of benzodiazepine use during pregnancy, which were adjusted for confounding exposures to alcohol, tobacco, and other medications, have not confirmed these findings.

8.2 Lactation

Risk Summary

Limited data from published literature reports the presence of alprazolam in human breast milk. There are reports of sedation, poor feeding and poor weight gain in infants exposed to benzodiazepines through breast milk. The effects of alprazolam on lactation are unknown.

Because of the potential for serious adverse reactions, including sedation and withdrawal symptoms in breastfed infants, advise patients that breastfeeding is not recommended during treatment with XANAX XR.

8.4 Pediatric Use

Safety and effectiveness of XANAX XR have not been established in pediatric patients.

8.5 Geriatric Use

XANAX XR treated geriatric patients had higher plasma concentrations of alprazolam (due to reduced clearance) compared to younger adults receiving the same doses. Therefore, dosage reduction of XANAX XR is recommended in geriatric patients [see Dosage and Administration (2.3) and Clinical Pharmacology (12.3)].

8.6 Hepatic Impairment

Patients with alcoholic liver disease exhibit a longer elimination half-life (19.7 hours), compared to healthy subjects (11.4 hours). This may be caused by decreased clearance of alprazolam in patients with alcoholic liver disease. Dosage reduction of XANAX XR is recommended in patients with hepatic impairment [see Dosage and Administration (2.4), Clinical Pharmacology (12.3)].

9 DRUG ABUSE AND DEPENDENCE

9.1 Controlled Substance

XANAX XR contains alprazolam, which is a Schedule IV controlled substance.

9.2 Abuse

XANAX XR is a benzodiazepine and a CNS depressant with a potential for abuse and addiction. Abuse is the intentional, non-therapeutic use of a drug, even once, for its desirable psychological or physiological effects. Misuse is the intentional use, for therapeutic purposes, of a drug by an individual in a way other than prescribed by a health care provider or for whom it was not prescribed. Drug addiction is a cluster of behavioral, cognitive, and physiological phenomena that may include a strong desire to take the drug, difficulties in controlling drug use (e.g., continuing drug use despite harmful consequences, giving a higher priority to drug use than other activities and obligations), and possible tolerance or physical dependence. Even taking benzodiazepines as prescribed may put patients at risk for abuse and misuse of their medication. Abuse and misuse of benzodiazepines may lead to addiction.

Abuse and misuse of benzodiazepines often (but not always) involve the use of doses greater than the maximum recommended dosage and commonly involve concomitant use of other medications, alcohol, and/or illicit substances, which is associated with an increased frequency of serious adverse outcomes, including respiratory depression, overdose, or death. Benzodiazepines are often sought by individuals who abuse drugs and other substances, and by individuals with addictive disorders [see Warnings and Precautions (5.2)].

The following adverse reactions have occurred with benzodiazepine abuse and/or misuse: abdominal pain, amnesia, anorexia, anxiety, aggression, ataxia, blurred vision, confusion, depression, disinhibition, disorientation, dizziness, euphoria, impaired concentration and memory, indigestion, irritability, muscle pain, slurred speech, tremors, and vertigo.

The following severe adverse reactions have occurred with benzodiazepine abuse and/or misuse: delirium, paranoia, suicidal ideation and behavior, seizures, coma, breathing difficulty, and death. Death is more often associated with polysubstance use (especially benzodiazepines with other CNS depressants such as opioids and alcohol).

9.3 Dependence

Physical Dependence

XANAX XR may produce physical dependence from continued therapy. Physical dependence is a state that develops as a result of physiological adaptation in response to repeated drug use, manifested by withdrawal signs and symptoms after abrupt discontinuation or a significant dose reduction of a drug. Abrupt discontinuation or rapid dosage reduction of benzodiazepines or administration of flumazenil, a benzodiazepine antagonist, may precipitate acute withdrawal reactions, including seizures, which can be life-threatening. Patients at an increased risk of withdrawal adverse reactions after benzodiazepine discontinuation or rapid dosage reduction include those who take higher dosages (i.e., higher and/or more frequent doses) and those who have had longer durations of use [see Warnings and Precautions (5.3)].

To reduce the risk of withdrawal reactions, use a gradual taper to discontinue XANAX XR or reduce the dosage [see Dosage and Administration (2.3), Warnings and Precautions (5.3)].

Acute withdrawal signs and symptoms associated with benzodiazepines have included abnormal involuntary movements, anxiety, blurred vision, depersonalization, depression, derealization, dizziness, fatigue, gastrointestinal adverse reactions (e.g., nausea, vomiting, diarrhea, weight loss, decreased appetite), headache, hyperacusis, hypertension, irritability, insomnia, memory impairment, muscle pain and stiffness, panic attacks, photophobia, restlessness, tachycardia, and tremor. More severe acute withdrawal signs and symptoms, including life-threatening reactions, have included catatonia, convulsions, delirium tremens, depression, hallucinations, mania, psychosis, seizures, and suicidality.

Protracted withdrawal syndrome associated with benzodiazepines is characterized by anxiety, cognitive impairment, depression, insomnia, formication, motor symptoms (e.g., weakness, tremor, muscle twitches), paresthesia, and tinnitus that persists beyond 4 to 6 weeks after initial benzodiazepine withdrawal. Protracted withdrawal symptoms may last weeks to more than 12 months. As a result, there may be difficulty in differentiating withdrawal symptoms from potential re-emergence or continuation of symptoms for which the benzodiazepine was being used.

Tolerance

Tolerance to XANAX XR may develop from continued therapy. Tolerance is a physiological state characterized by a reduced response to a drug after repeated administration (i.e., a higher dose of a drug is required to produce the same effect that was once obtained at a lower dose). Tolerance to the therapeutic effect of XANAX XR may develop; however, little tolerance develops to the amnestic reactions and other cognitive impairments caused by benzodiazepines.

10 OVERDOSAGE

Overdosage of benzodiazepines is characterized by central nervous system depression ranging from drowsiness to coma. In mild to moderate cases, symptoms can include drowsiness, confusion, dysarthria, lethargy, hypnotic state, diminished reflexes, ataxia, and hypotonia. Rarely, paradoxical or disinhibitory reactions (including agitation, irritability, impulsivity, violent behavior, confusion, restlessness, excitement, and talkativeness) may occur. In severe overdosage cases, patients may develop respiratory depression and coma. Overdosage of benzodiazepines in combination with other CNS depressants (including alcohol and opioids) may be fatal [see Warnings and Precautions (5.2)]. Markedly abnormal (lowered or elevated) blood pressure, heart rate, or respiratory rate raise the concern that additional drugs and/or alcohol are involved in the overdosage.

In managing benzodiazepine overdosage, employ general supportive measures, including intravenous fluids and airway management. Flumazenil, a specific benzodiazepine receptor antagonist indicated for the complete or partial reversal of the sedative effects of benzodiazepines in the management of benzodiazepine overdosage, can lead to withdrawal and adverse reactions, including seizures, particularly in the context of mixed overdosage with drugs that increase seizure risk (e.g., tricyclic and tetracyclic antidepressants) and in patients with long-term benzodiazepine use and physical dependency. The risk of withdrawal seizures with flumazenil use may be increased in patients with epilepsy. Flumazenil is contraindicated in patients who have received a benzodiazepine for control of a potentially life-threatening condition (e.g., status epilepticus). If the decision is made to use flumazenil, it should be used as an adjunct to, not as a substitute for, supportive management of benzodiazepine overdosage. See the flumazenil injection Prescribing Information.

Consider contacting the Poison Help Line at (1-800-222-1222), or a medical toxicologist for additional overdosage management recommendations.

11 DESCRIPTION

XANAX XR contains alprazolam which is a triazolo analog of the 1,4 benzodiazepine class of central nervous system-active compounds.

The chemical name of alprazolam is 8-chloro-1-methyl-6-phenyl-4H-s-triazolo [4,3-α] [1,4] benzodiazepine. The molecular formula is C17H13ClN4 which corresponds to a molecular weight of 308.76.

The structural formula is represented below:

Alprazolam is a white crystalline powder, which is soluble in methanol or ethanol but which has no appreciable solubility in water at physiological pH.

Each XANAX XR extended-release tablet, for oral administration, contains 0.5 mg, 1 mg, 2 mg, or 3 mg of alprazolam. The inactive ingredients are colloidal silicon dioxide, hypromellose, lactose, and magnesium stearate. In addition, the 1 mg and 3 mg tablets contain D & C yellow No. 10 and the 2 mg and 3 mg tablets contain FD&C blue No. 2.

12 CLINICAL PHARMACOLOGY

12.1 Mechanism of Action

Alprazolam is a 1,4 benzodiazepine. Alprazolam exerts its effect for the treatment of panic disorder through binding to the benzodiazepine site of gamma aminobutyric acid-A (GABAA) receptors in the brain and enhances GABA-mediated synaptic inhibition.

12.3 Pharmacokinetics

The pharmacokinetics of alprazolam and two of its major active metabolites (4-hydroxyalprazolam and α-hydroxyalprazolam) are linear, and concentrations are proportional up to 10 mg XANAX XR given once daily.

Absorption

Following oral administration of XANAX XR in the morning, peak plasma concentration of alprazolam (Cmax) occurs in about 10 hours postdose. Compared to morning dosing, alprazolam Cmax increased by 30% and the Tmax decreased by an hour following dosing at night.

The mean absolute bioavailability of alprazolam following administration of XANAX XR is approximately 90%, and the relative bioavailability compared to XANAX is about 100%. The bioavailability and pharmacokinetics of alprazolam following administration of XANAX XR are similar to that for XANAX, with the exception of a slower rate of absorption.

Effect of Food

A high-fat meal given up to 2 hours before dosing with XANAX XR increased the mean Cmax by about 25%. The effect of this meal on Tmax depended on the timing of the meal, with a reduction in Tmax by about 1/3 for subjects eating immediately before dosing and an increase in Tmax by about 1/3 for subjects eating 1 hour or more after dosing. The extent of exposure (AUC) and elimination half-life (t½) were not affected by eating.

Distribution

The apparent volume of distribution of alprazolam is similar for XANAX XR and XANAX. Alprazolam is 80% bound to human serum protein, and albumin accounts for the majority of the binding.

Elimination

The mean plasma elimination half-life of alprazolam following administration of XANAX XR ranges from 10.7 to 15.8 hours in healthy adults.

Metabolism

Alprazolam is extensively metabolized in humans, primarily by cytochrome P450 3A4 (CYP3A4), to two major active metabolites in the plasma: 4-hydroxyalprazolam and α-hydroxyalprazolam. The plasma circulation levels of the two active metabolites after both XANAX XR and XANAX are less than 10% and 4% of the parent, respectively. The reported relative potencies in benzodiazepine receptor binding experiments and in animal models of induced seizure inhibition are 0.20 and 0.66, respectively, for 4-hydroxyalprazolam and α-hydroxyalprazolam. The low concentrations and low potencies of 4-hydroxyalprazolam and α-hydroxyalprazolam indicate that they unlikely contribute much to the effects of alprazolam. A benzophenone derived from alprazolam is also found in humans. Their half-lives appear to be similar to that of alprazolam. The pharmacokinetic parameters at steady-state for the two hydroxylated metabolites of alprazolam (4-hydroxyalprazolam and α-hydroxyalprazolam) were similar for XANAX and XANAX XR, indicating that the metabolism of alprazolam is not affected by absorption rate.

Excretion

Alprazolam and its metabolites are excreted primarily in the urine.

Specific Populations

Geriatric Patients

The mean T1/2 of alprazolam was 16.3 hours (range: 9.0 to 26.9 hours) in healthy elderly subjects compared to 11.0 hours (range: 6.3 to 15.8 hours, n=16) in healthy adult subjects.

Obese Patients

The mean T1/2 of alprazolam was 21.8 hours (range: 9.9 to 40.4 hours) in a group of obese subjects.

Patients with Hepatic Impairment

The mean T1/2 of alprazolam was 19.7 hours (range: 5.8 to 65.3 hours) in patients with alcoholic liver disease.

Racial or Ethnic Groups

Maximal concentrations and T1/2 of alprazolam are approximately 15% and 25% higher in Asians compared to Caucasians.

Smoking

Alprazolam concentrations may be reduced by up to 50% in smokers compared to non-smokers.

Drug Interaction Studies

In Vivo Studies

Most of the interactions that have been documented with alprazolam are with drugs that modulate CYP3A4 activity.

Compounds that are inhibitors or inducers of CYP3A would be expected to increase or decrease plasma alprazolam concentrations, respectively. Drug products that have been studied in vivo, along with their effect on increasing alprazolam AUC, are as follows: ketoconazole, 3.98 fold; itraconazole, 2.66 fold; nefazodone, 1.98 fold; fluvoxamine, 1.96 fold; and erythromycin, 1.61 fold [see Contraindications (4), Warnings and Precautions (5.5), Drug Interactions (7.2)]. Other studied drugs include:

Cimetidine: Coadministration of cimetidine increased the maximum plasma concentration of alprazolam by 82%, decreased clearance by 42%, and increased T1/2 by 16%.

Fluoxetine: Coadministration of fluoxetine with alprazolam increased the maximum plasma concentration of alprazolam by 46%, decreased clearance by 21%, increased T1/2 by 17%, and decreased measured psychomotor performance.

Oral Contraceptives: Coadministration of oral contraceptives increased the maximum plasma concentration of alprazolam by 18%, decreased clearance by 22%, and increased T1/2 by 29%.

Carbamazepine: The oral clearance of alprazolam (given in a 0.8 mg single dose) was increased from 0.90±0.21 mL/min/kg to 2.13±0.54 mL/min/kg and the elimination T1/2 was shortened (from 17.1±4.9 to 7.7 ±1.7 hour) following administration of 300 mg per day carbamazepine for 10 days [see Drug Interactions (7.2)]. However, the carbamazepine dose used in this study was fairly low compared to the recommended doses (1000 1200 mg per day); the effect at usual carbamazepine doses is unknown.

Ritonavir: Interactions involving HIV protease inhibitors (e.g., ritonavir) and alprazolam are complex and time dependent. Short-term low doses of ritonavir (4 doses of 200 mg) increased mean AUC of alprazolam by about 2.5-fold, and did not significantly affect Cmax of alprazolam. The elimination T1/2 was prolonged (30 hours versus 13 hours). However, upon extended exposure to ritonavir (500 mg, twice daily for 10 days), CYP3A induction offset this inhibition. Alprazolam AUC and Cmax was reduced by 12% and 16%, respectively, in the presence of ritonavir. The elimination T1/2 of alprazolam was not significantly changed [see Warnings and Precautions (5.5)].

Sertraline: A single dose of alprazolam 1 mg and steady state dose of sertraline (50 to 150 mg per day) did not reveal any clinically significant changes in the pharmacokinetics of alprazolam.

Imipramine and Desipramine: The steady state plasma concentrations of imipramine and desipramine have been reported to be increased an average of 31% and 20%, respectively, by the concomitant administration of XANAX in doses up to 4 mg per day.

Warfarin: Alprazolam did not affect the prothrombin or plasma warfarin levels in male volunteers administered sodium warfarin orally.

In Vitro Studies

Data from in vitro studies of alprazolam suggest a possible drug interaction of alprazolam with paroxetine. The ability of alprazolam to induce human hepatic enzyme systems has not been determined.

13 NONCLINICAL TOXICOLOGY

13.1 Carcinogenesis, Mutagenesis, Impairment of Fertility

Carcinogenesis

No evidence of carcinogenic potential was observed in rats or mice administered alprazolam for 2 years at doses up to 30 and 10 mg/kg/day, respectively. These doses are 29 times and 4.8 times the maximum recommended human dose of 10 mg/day based on mg/m2 body surface area, respectively.

Mutagenesis

Alprazolam was negative in the in vitro Ames bacterial reverse mutation assay and DNA Damage/Alkaline Elution Assay and in vivo rat micronucleus genetic toxicology assays.

Impairment of Fertility

Alprazolam produced no impairment of fertility in rats at doses up to 5 mg/kg per day, which is approximately 5 times the maximum recommended human dose of 10 mg per day based on mg/m2 body surface area.

13.2 Animal Toxicology and/or Pharmacology

When rats were treated with alprazolam at oral doses of 3 mg/kg, 10 mg/kg, and 30 mg/kg per day (3 to 29 times the maximum recommended human dose based on mg/m^2 body surface area) for 2 years, a tendency for a dose related increase in the number of cataracts was observed in females and a tendency for a dose related increase in corneal vascularization was observed in males. These lesions did not appear until after 11 months of treatment.

14 CLINICAL STUDIES

The efficacy of XANAX XR in the treatment of panic disorder in adults was established in two 6-week, flexible-dose, placebo-controlled studies in adult patients meeting DSM-III criteria for panic disorder. In these studies, patients were treated with XANAX XR in a dose range of 1 mg to 10 mg once per day. The effectiveness of XANAX XR was assessed on the basis of changes in various measures of panic attack frequency, on various measures of the Clinical Global Impression, and on the Overall Phobia Scale. In all, there were 7 primary efficacy measures in these studies, and XANAX XR was superior to placebo on all 7 outcomes in both studies. The mean dose of XANAX XR at the last treatment visit was 4.2 mg per day in the first study and 4.6 mg per day in the second.

In addition, there were two 8-week, fixed-dose, placebo-controlled studies of XANAX XR in adult patients with panic disorder, involving fixed XANAX XR doses of 4 mg and 6 mg once per day that did not show a benefit for either dose of XANAX XR.

Analyses of the relationship between treatment outcome and gender did not suggest any differential responsiveness on the basis of gender.

16 HOW SUPPLIED/STORAGE AND HANDLING

XANAX XR is supplied in the following strengths and package configurations:

XANAX XR Tablets
Package Configuration | Tablet Strength (mg) | NDC | Print
Bottles of 60 | 0.5 mg | NDC 58151-503-91 | white, pentagonal shaped tablets debossed with an "X" on one side and "0.5" on the other side
Bottles of 60 | 1 mg | NDC 58151-504-91 | yellow, square shaped tablets debossed with an "X" on one side and "1" on the other side
Bottles of 60 | 2 mg | NDC 58151-505-91 | blue, round shaped tablets debossed with an "X" on one side and "2" on the other side
Bottles of 60 | 3 mg | NDC 58151-506-91 | green, triangular shaped tablets debossed with an "X" on one side and "3" on the other side

Store at 20°C to 25°C (68°F to 77°F); excursions permitted to 15–30°C (59–86°F) [see USP Controlled Room Temperature].

17 PATIENT COUNSELING INFORMATION

Advise the patient to read the FDA-approved patient labeling (Medication Guide).

Risks from Concomitant Use with Opioids

Advise both patients and caregivers about the risks of potentially fatal respiratory depression and sedation when XANAX XR is used with opioids and not to use such drugs concomitantly unless supervised by a healthcare provider. Advise patients not to drive or operate heavy machinery until the effects of concomitant use with the opioid have been determined [see Warnings and Precautions (5.1), Drug Interactions (7.1)].

Abuse, Misuse, and Addiction

Inform patients that the use of XANAX XR, even at recommended dosages, exposes users to risks of abuse, misuse, and addiction, which can lead to overdose and death, especially when used in combination with other medications (e.g., opioid analgesics), alcohol, and/or illicit substances. Inform patients about the signs and symptoms of benzodiazepine abuse, misuse, and addiction; to seek medical help if they develop these signs and/or symptoms; and on the proper disposal of unused drug [see Warnings and Precautions (5.2), Drug Abuse and Dependence (9.2)].

Withdrawal Reactions

Inform patients that the continued use of XANAX XR may lead to clinically significant physical dependence and that abrupt discontinuation or rapid dosage reduction of XANAX XR may precipitate acute withdrawal reactions, which can be life-threatening. Inform patients that in some cases, patients taking benzodiazepines have developed a protracted withdrawal syndrome with withdrawal symptoms lasting weeks to more than 12 months. Instruct patients that discontinuation or dosage reduction of XANAX XR may require a slow taper [see Warnings and Precautions (5.3), Drug Abuse and Dependence (9.3)].

Effects on Driving and Operating Machinery

Advise patients not to drive a motor vehicle or operate heavy machinery while taking XANAX XR due to its CNS depressant effects. Also advise patients to avoid use of alcohol or other CNS depressants while taking XANAX XR [see Warnings and Precautions (5.3)].

Patients with Depression

Advise patients, their families and caregivers to look for signs of suicidality or worsening depression, and to inform the patient’s healthcare provider immediately [see Warnings and Precautions (5.6)].

Concomitant Medications

Advise patients to inform their healthcare provider of all medicines they take, including prescription and nonprescription medications, vitamins and herbal supplements [see Drug Interactions (7)].

Pregnancy

Advise pregnant females that use of XANAX XR late in pregnancy can result in sedation (respiratory depression, lethargy, hypotonia) and/or withdrawal symptoms (hyperreflexia, irritability, restlessness, tremors, inconsolable crying, and feeding difficulties) in newborns [see Warnings and Precautions (5.8), Use in Specific Populations (8.1)]. Instruct patients to inform their healthcare provider if they are pregnant.

Advise patients that there is a pregnancy exposure registry that monitors pregnancy outcomes in women exposed to XANAX XR during pregnancy [see Use in Specific Populations (8.1)].

Lactation

Advise patients that breastfeeding is not recommended during treatment with XANAX XR [see Use in Specific Populations (8.2)].

Distributed by:
Viatris Specialty LLC
Morgantown, WV 26505 U.S.A.

Made in Ireland

© 2023 Viatris Inc.

XANAX XR is a registered trademark of UPJOHN US 2 LLC, a Viatris Company.

UPJ:XNXXRT:R1

Medication Guide

XANAX XR (ZAN-aks XR)
(alprazolam) extended-release tablets, C-IV

What is the most important information I should know about XANAX XR?

- XANAX XR is a benzodiazepine medicine. Taking benzodiazepines with opioid medicines, alcohol, or other central nervous system (CNS) depressants (including street drugs) can cause severe drowsiness, breathing problems (respiratory depression), coma and death. Get emergency help right away if any of the following happens:
  - shallow or slowed breathing
  - breathing stops (which may lead to the heart stopping)
  - excessive sleepiness (sedation)
    Do not drive or operate heavy machinery until you know how taking XANAX XR with opioids affects you.
- Risk of abuse, misuse, and addiction. There is a risk of abuse, misuse, and addiction with benzodiazepines including XANAX XR which can lead to overdose and serious side effects including coma and death.
  - Serious side effects including coma and death have happened in people who have abused or misused benzodiazepines, including XANAX XR. These serious side effects may also include delirium, paranoia, suicidal thoughts or actions, seizures, and difficulty breathing. Call your healthcare provider or go to the nearest hospital emergency room right away if you get any of these serious side effects.
  - You can develop an addiction even if you take XANAX XR as prescribed by your healthcare provider.
  - Take XANAX XR exactly as your healthcare provider prescribed.
  - Do not share your XANAX XR with other people.
  - Keep XANAX XR in a safe place and away from children.
- Physical dependence and withdrawal reactions. XANAX XR can cause physical dependence and withdrawal reactions.
  - Do not suddenly stop taking XANAX XR. Stopping XANAX XR suddenly can cause serious and life-threatening side effects, including unusual movements, responses, or expressions, seizures, sudden and severe mental or nervous system changes, depression, seeing or hearing things that others do not see or hear, an extreme increase in activity or talking, losing touch with reality, and suicidal thoughts or actions. Call your healthcare provider or go to the nearest hospital emergency room right away if you get any of the following symptoms.
  - Some people who suddenly stop benzodiazepines, have symptoms that can last for several weeks to more than 12 months, including anxiety, trouble remembering, learning, or concentrating, depression, problems sleeping, feeling like insects are crawling under your skin, weakness, shaking, muscle twitching, burning or prickling feeling in your hands, arms, legs or feet, and ringing in your ears.
  - Physical dependence is not the same as drug addiction. Your healthcare provider can tell you more about the differences between physical dependence and drug addiction.
  - Do not take more XANAX XR than prescribed or take XANAX XR for longer than prescribed.

What is XANAX XR?

- XANAX XR is a prescription medicine used to treat panic disorder, with or without a fear of places and situations that might cause panic, helplessness, or embarrassment (agoraphobia).
- XANAX XR is a federal controlled substance (C-IV) because it contains alprazolam that can be abused or lead to dependence. Keep XANAX XR in a safe place to prevent misuse and abuse. Selling or giving away XANAX XR may harm others and is against the law. Tell your healthcare provider if you have abused or been dependent on alcohol, prescription medicines or street drugs.
- It is not known if XANAX XR is safe and effective in children.
- Elderly patients are especially susceptible to dose related adverse effects when taking XANAX XR.
- It is not known if XANAX XR is safe and effective in the treatment of panic disorder for use longer than 8 weeks.

Do not take XANAX XR if:

- you are allergic to alprazolam, other benzodiazepines, or any of the ingredients in XANAX XR. See the end of this Medication Guide for a complete list of ingredients in XANAX XR.
- you are taking antifungal medicines including ketoconazole and itraconazole

Before you take XANAX XR, tell your healthcare provider about all of your medical conditions, including if you:

- have or have had depression, mood problems, or suicidal thoughts or behavior
- have liver or kidney problems
- have lung disease or breathing problems
- are pregnant or plan to become pregnant.
  - Taking XANAX XR late in pregnancy may cause your baby to have symptoms of sedation (breathing problems, sluggishness, low muscle tone), and/or withdrawal symptoms (jitteriness, irritability, restlessness, shaking, excessive crying, feeding problems).
  - Tell your healthcare provider right away if you become pregnant or think you are pregnant during treatment with XANAX XR.
  - There is a pregnancy registry for women who take XANAX XR during pregnancy. The purpose of the registry is to collect information about the health of you and your baby. If you become pregnant during treatment with XANAX XR, talk to your healthcare provider about registering with the National Pregnancy Registry for Psychiatric Medications. You can register by calling 1-866-961-2388 or visiting https://womensmentalhealth.org/research/pregnancyregistry/.
- are breastfeeding or plan to breastfeed. XANAX XR passes into your breast milk.
  - Talk to your healthcare provider about the best way to feed your baby if you take XANAX XR.
  - Breastfeeding is not recommended during treatment with XANAX XR.

Tell your healthcare provider about all the medicines you take, including prescription and over-the-counter medicines, vitamins, and herbal supplements.

Taking XANAX XR with certain other medicines can cause side effects or affect how well XANAX XR or the other medicines work. Do not start or stop other medicines without talking to your healthcare provider.

How should I take XANAX XR?

- See “What is the most important information I should know about XANAX XR?”
- Take XANAX XR exactly as your healthcare provider tells you to take it. Your healthcare provider will tell you how much XANAX XR to take and when to take it.
- If you take too much XANAX XR, call your healthcare provider or go to the nearest hospital emergency room right away.
- Swallow XANAX XR tablets whole. Do not crush, chew or break XANAX XR.

What are the possible side effects of XANAX XR?

XANAX XR may cause serious side effects, including:

- See “What is the most important information I should know about XANAX XR?”
- Seizures. Stopping XANAX XR can cause seizures and seizures that will not stop (status epilepticus).
- Mania. XANAX XR may cause an increase in activity and talking (hypomania and mania) in people who have depression.
- XANAX XR can make you sleepy or dizzy and can slow your thinking and motor skills.
  - Do not drive, operate heavy machinery, or do other dangerous activities until you know how XANAX XR affects you.
  - Do not drink alcohol or take other drugs that may make you sleepy or dizzy while taking XANAX XR without first talking to your healthcare provider. When taken with alcohol or drugs that cause sleepiness or dizziness, XANAX XR may make your sleepiness or dizziness much worse.

The most common side effects of XANAX XR include:

- sleepiness
- trouble saying words clearly (dysarthria)
- problems with memory
- problems with coordination

- changes in sex drive (libido)
- constipation
- nausea

These are not all the possible side effects of XANAX XR. Call your doctor for medical advice about side effects. You may report side effects to FDA at 1-800-FDA-1088.

How should I store XANAX XR?

- Store XANAX XR at room temperature between 68°F to 77°F (20°C to 25°C)
- Keep XANAX XR and all medicines out of the reach of children.

General information about the safe and effective use of XANAX XR.

- Medicines are sometimes prescribed for purposes other than those listed in a Medication Guide.
- Do not use XANAX XR for a condition for which it was not prescribed.
- Do not give XANAX XR to other people, even if they have the same symptoms that you have. It may harm them.
- You can ask your pharmacist or healthcare provider for information about XANAX XR that is written for health professionals.

What are the ingredients in XANAX XR?

Active ingredient: alprazolam

Inactive ingredients: lactose, magnesium stearate, colloidal silicon dioxide, and hypromellose. In addition, the 1 mg and 3 mg tablets contain D & C yellow No. 10 and the 2 mg and 3 mg tablets contain FD&C blue No. 2.

For more information, call Viatris at 1-877-446-3679 (1-877-4-INFO-RX).

Distributed by:

Viatris Specialty LLC

Morgantown, WV 26505 U.S.A.

Made in Ireland

© 2023 Viatris Inc.

XANAX XR is a registered trademark of UPJOHN US 2 LLC, a Viatris Company.

UPJ:MG:XNXXRT:R1

This Medication Guide has been approved by the U.S. Food and Drug Administration. Revised: 4/2023

PRINCIPAL DISPLAY PANEL – 0.5 mg

ALWAYS DISPENSE WITH MEDICATION GUIDE

NDC 58151-503-91

Xanax XR® CIV

alprazolam
extended-release tablets

0.5 mg

60 Tablets

Rx only

VIATRIS

Store at 20°C to 25°C
(68°F to 77°F);
excursions permitted to
15–30°C (59–86°F)
[see USP Controlled Room
Temperature].

Dispense in tight (USP),
child-resistant containers.

DOSAGE AND USE
See accompanying
prescribing information.

Each tablet contains
0.5 mg alprazolam.

Distributed by:
Viatris Specialty LLC
Morgantown, WV 26505 U.S.A.

Made in Ireland

© 2025 Viatris Inc.

RUPJ503D1

PRINCIPAL DISPLAY PANEL – 1 mg

ALWAYS DISPENSE WITH MEDICATION GUIDE

NDC 58151-504-91

Xanax XR® CIV

alprazolam
extended-release tablets

1 mg

60 Tablets

Rx only

VIATRIS

Store at 20°C to 25°C
(68°F to 77°F);
excursions permitted to
15–30°C (59–86°F)
[see USP Controlled Room
Temperature].

Dispense in tight (USP),
child-resistant containers.

DOSAGE AND USE
See accompanying
prescribing information.

Each tablet contains
1 mg alprazolam.

Distributed by:
Viatris Specialty LLC
Morgantown, WV 26505 U.S.A.

Made in Ireland

© 2025 Viatris Inc.

RUPJ504D1

PRINCIPAL DISPLAY PANEL – 2 mg

ALWAYS DISPENSE WITH MEDICATION GUIDE

NDC 58151-505-91

Xanax XR® CIV

alprazolam
extended-release tablets

2 mg

60 Tablets

Rx only

VIATRIS

Store at 20°C to 25°C
(68°F to 77°F);
excursions permitted to
15–30°C (59–86°F)
[see USP Controlled Room
Temperature].

Dispense in tight (USP),
child-resistant containers.

DOSAGE AND USE
See accompanying
prescribing information.

Each tablet contains
2 mg alprazolam.

Distributed by:
Viatris Specialty LLC
Morgantown, WV 26505 U.S.A.

Made in Ireland

© 2025 Viatris Inc.

RUPJ505D1

PRINCIPAL DISPLAY PANEL – 3 mg

ALWAYS DISPENSE WITH MEDICATION GUIDE

NDC 58151-506-91

Xanax XR® CIV

alprazolam
extended-release tablets

3 mg

60 Tablets

Rx only

VIATRIS

Store at 20°C to 25°C
(68°F to 77°F);
excursions permitted to
15–30°C (59–86°F)
[see USP Controlled Room
Temperature].

Dispense in tight (USP),
child-resistant containers.

DOSAGE AND USE
See accompanying
prescribing information.

Each tablet contains
3 mg alprazolam.

Distributed by:
Viatris Specialty LLC
Morgantown, WV 26505 U.S.A.

Made in Ireland

© 2025 Viatris Inc.

RUPJ506D1